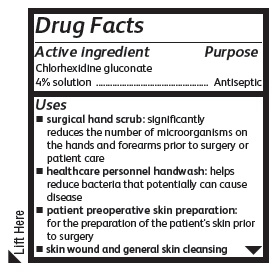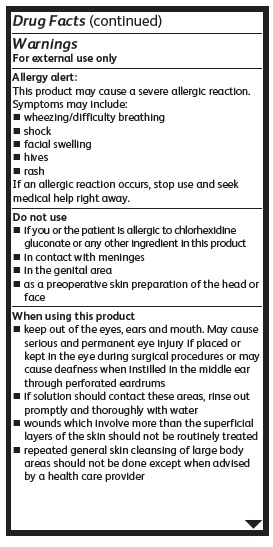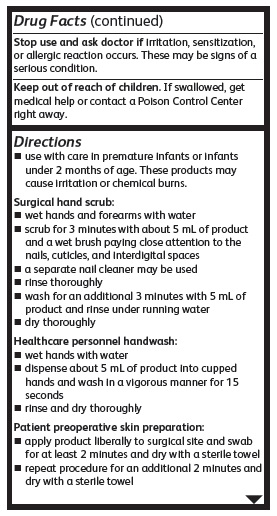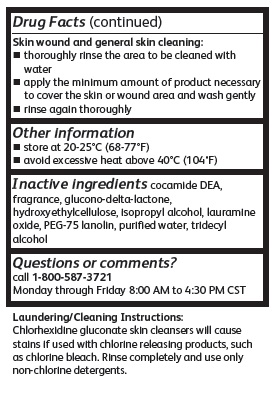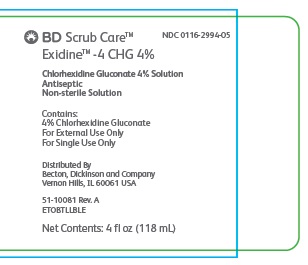 DRUG LABEL: Scrub Care
NDC: 0116-2994 | Form: LIQUID
Manufacturer: Xttrium Laboratories, Inc.
Category: otc | Type: HUMAN OTC DRUG LABEL
Date: 20201021

ACTIVE INGREDIENTS: CHLORHEXIDINE GLUCONATE 4 mg/100 mL
INACTIVE INGREDIENTS: LAURAMINE OXIDE; COCO DIETHANOLAMIDE; GLUCONOLACTONE; HYDROXYETHYL CELLULOSE (2000 CPS AT 1%); TRIDECYL ALCOHOL; PEG-75 LANOLIN; WATER; ISOPROPYL ALCOHOL

Drug Facts CF ETO

Active Ingredient

Chlorhexidine Gluconate 4% Solution

Purposes

Antiseptic

Uses

- surgical hand scrub: significantly reduces the number of microorganisms on the hand and forearms prior to surgery or patient care
- healthcare personnel hand wash: helps reduce bacteria that potentially can cause disease
- patient preoperative skin preparation: preparation of the patient’s skin prior to surgery
- skin wound and general skin cleansing

Warnings

For external use only

Allergy alert:

This product may cause a severe allergic reaction. Symptoms may include:

- wheezing
- shock
- facial swelling
- hives
- rash

If an allergic reaction occurs, stop use and seek medical help right away

Do not use

- if you or the patient is allergic to chlorhexidine gluconate or any other ingredient in thus product
- in contact with meninges
- in genital area
- as a preoperative skin preparation of the head or face

when using this product

- keep out of eyes, ears, and mouth. May cause serious and permanent eye injury if permitted to enter and remain in the eye or may cause deafness when instilled in the middle ear through perforated eardrums
- if solution should contact these areas, rinse out promptly and thoroughly with water
- wounds which involve more than the superficial layers if the skin should not be routinely treated
- repeated general skin cleansing of large body areas should not be done except when advised by a health care provider

Stop use and ask doctor

If irritation, sensitization or allergic reaction occurs. These may be signs of a serious condition.

KEEP OUT OF REACH OF CHILDREN

If swallowed, get medical help or contact a Poison Control Center right away.

Direction

- use with care in premature infants or infants under 2 months of age. These products may cause irritation or chemical burns.

Surgical hand scrub:

- wet arms and forearms with water
- scrub for 3 minutes with about 5 ml of product and a wet brush paying close attention to the nails, cuticles, and interdigital spaces
- a separate nail cleaner may be used
- rinse thoroughly
- wash for an additional 3 minutes with 5 ml of product and rinse under running water
- dry thoroughly

Healthcare personnel handwash:

- wet hands water
- dispense about 5 ml of product into cupped hands and wash in a vigorous manner for 15 seconds
- rinse and dry thoroughly.

Patient preoperative skin preparation:

- apply product liberally to surgical site and swab for at least 2 minutes
- dry with a sterile towel
- repeat procedure for an additional 2 minutes and dry with a sterile towel

Skin wound and general skin cleansing:

- thoroughly rinse the area to be cleaned with water
- apply the minimum amount of product necessary to cover the skin or wound area and wash gently
- rinse again thoroughly

Other Information

- Store at 20-25º C (68-77ºF)
- Avoid excessive heat above 40ºC (104ºF)

Inactive Ingredients

cocamide DEA, fragrance, glucono-delta-lactone, hydroxyethylcellulose, isopropyl alcohol, lauramine oxide, PEG-75 lanolin, purified water, tridecyl alcohol.

Questions or comments?

Call 1-800-587-3721

Monday through Friday 8:00 AM to 4:30 PM CST

Principal Display Panel

NDC 0116-2994

BD Scrub Care™

Exidine™ - 4 CHG 4%

Chlorhexidine Gluconate 4% Solution

Antiseptic

Non-sterile Solution

Contains:

4% Chlorhexidine Gluconate

For External Use Only

For Single Use Only

Distributed By

Becton, Dickinson and Company

Vernon Hills, IL 60061 USA

51-10081 Rev. A

ETOBTLLBLE

Net Contents: 4 fl oz (118 mL)